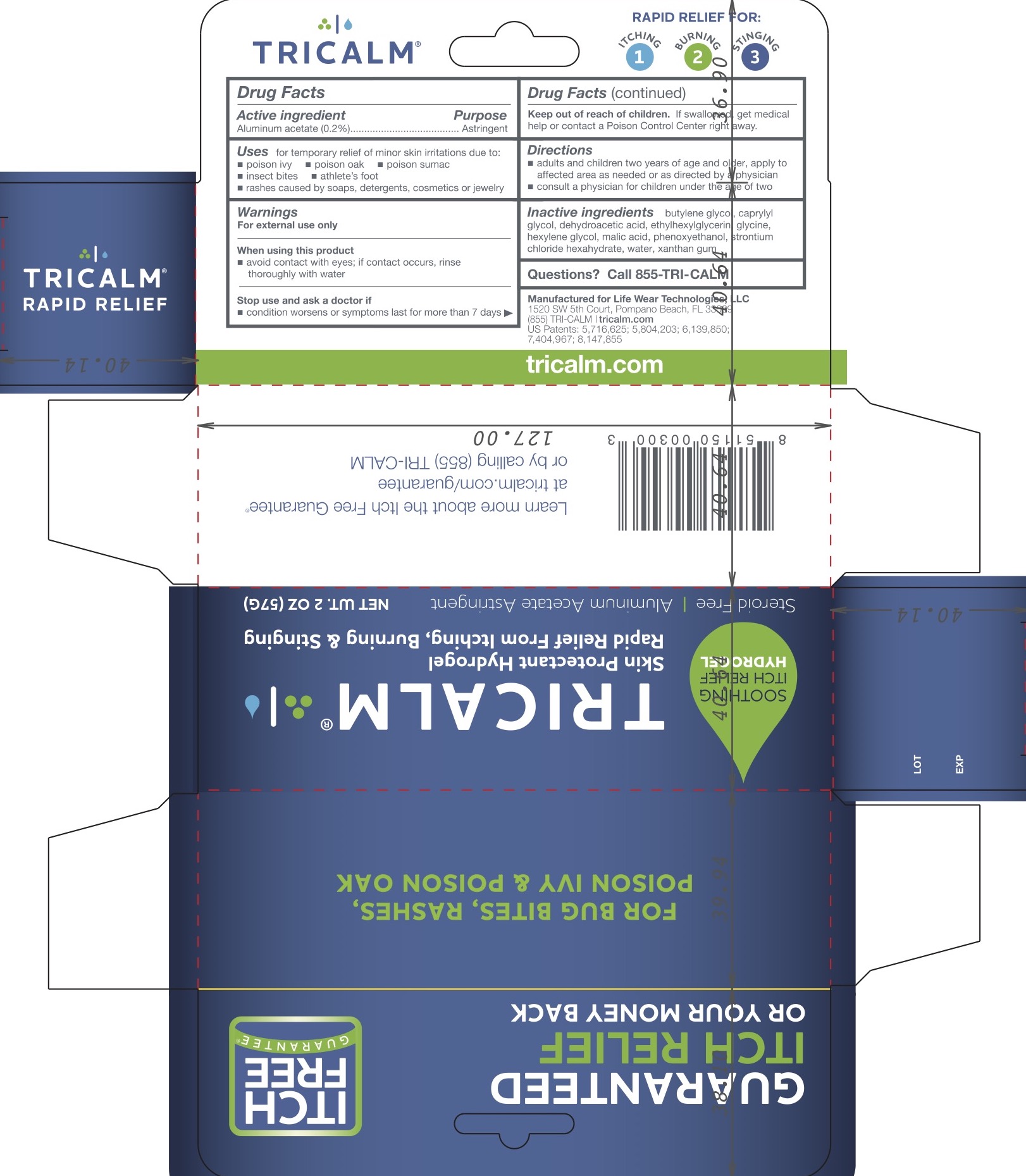 DRUG LABEL: Tricalm Hydrogel
NDC: 71207-221 | Form: GEL
Manufacturer: MODULAR THERMAL TECHNOLOGIES LLC DBA LIFE WEAR TECHNOLOGIES
Category: otc | Type: HUMAN OTC DRUG LABEL
Date: 20231020

ACTIVE INGREDIENTS: ALUMINUM ACETATE 0.2 g/100 g
INACTIVE INGREDIENTS: BUTYLENE GLYCOL; GLYCINE; HEXYLENE GLYCOL; PHENOXYETHANOL; CAPRYLYL GLYCOL; DEHYDROACETIC ACID; ETHYLHEXYLGLYCERIN; MALIC ACID; STRONTIUM CHLORIDE HEXAHYDRATE; WATER; XANTHAN GUM

Tricalm Hydrogel

ACTIVE INGREDIENT

Aluminum acetate 0.2%

PURPOSE

Astringent

INDICATIONS AND USAGE

For the temporary relief of minor skin irritations due to:

- poison ivy
- poison oak
- poison sumac
- insect bites
- rashes caused by soaps, detergents, cosmetics, or jewelry
- athlete's foot

WARNINGS

For external use only.

When using this product avoid contact with eyes; if contact occurs, rinse thoroughly with water

Stop use and ask a doctor if condition worsens or symptoms last for more than 7 days

KEEP OUT OF REACH OF CHILDREN

If swallowed, get medical help or contact a Poison Control Center right away.

DOSAGE AND ADMINISTRATION

- adults and children two years of age and older, apply to affected areas as needed or as directed by a physician
- consult a physician for children under the age of two

INACTIVE INGREDIENT

butylene glycol, caprylyl glycol, dehydroacetic acid, ethylhexylglycerin, glycine, hexylene glycol, malic acid, phenoxyethanol, strontium chloride hexahydrate, water, xanthan gum